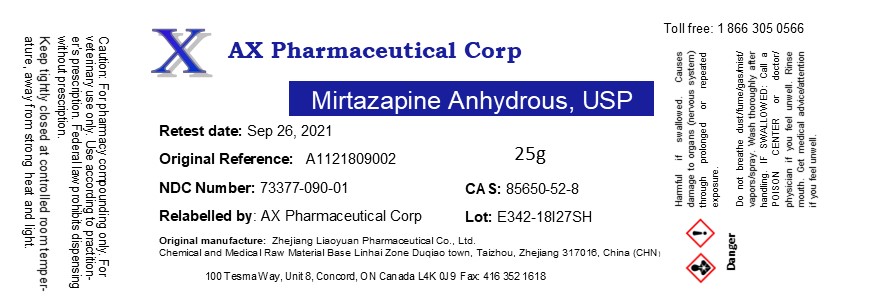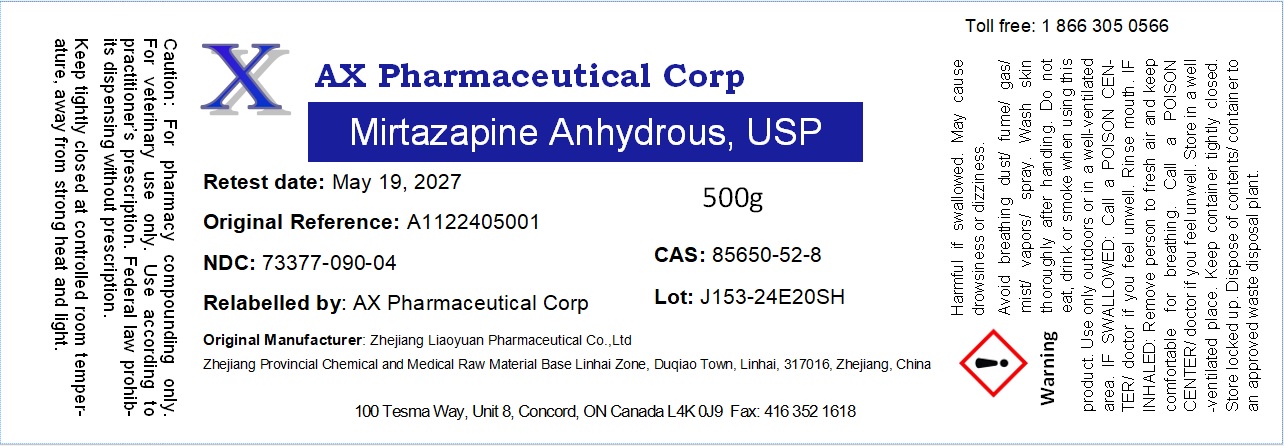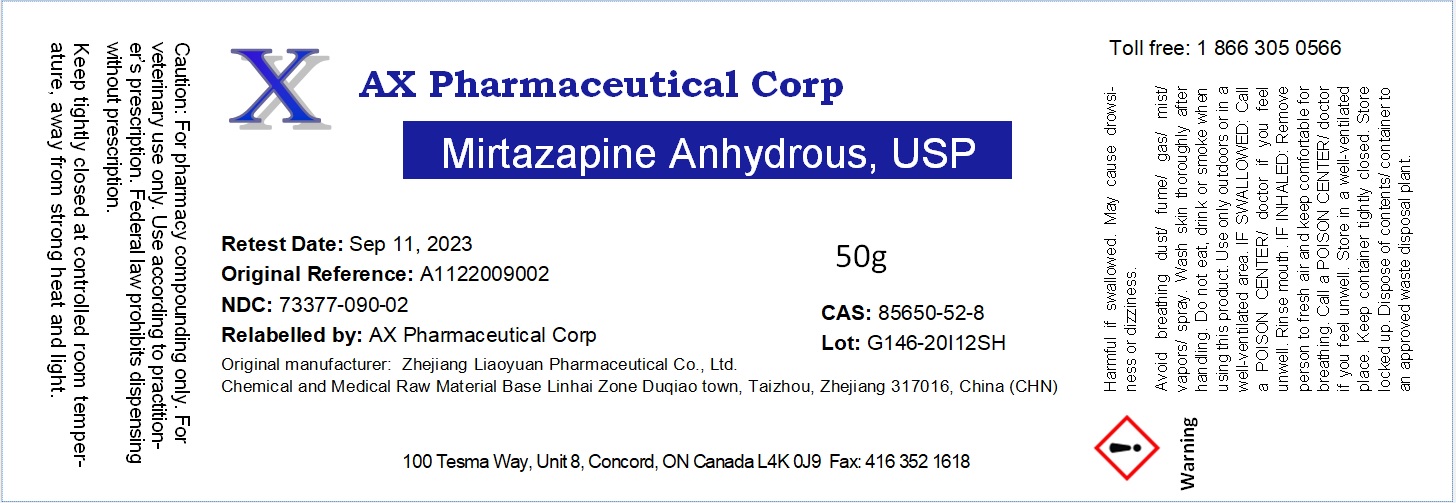 DRUG LABEL: Mirtazapine Anhydrous
NDC: 73377-090 | Form: POWDER
Manufacturer: AX Pharmaceutical Corp
Category: other | Type: BULK INGREDIENT - ANIMAL DRUG
Date: 20241017

ACTIVE INGREDIENTS: MIRTAZAPINE 1 g/1 g

Mirtazapine Anhydrous